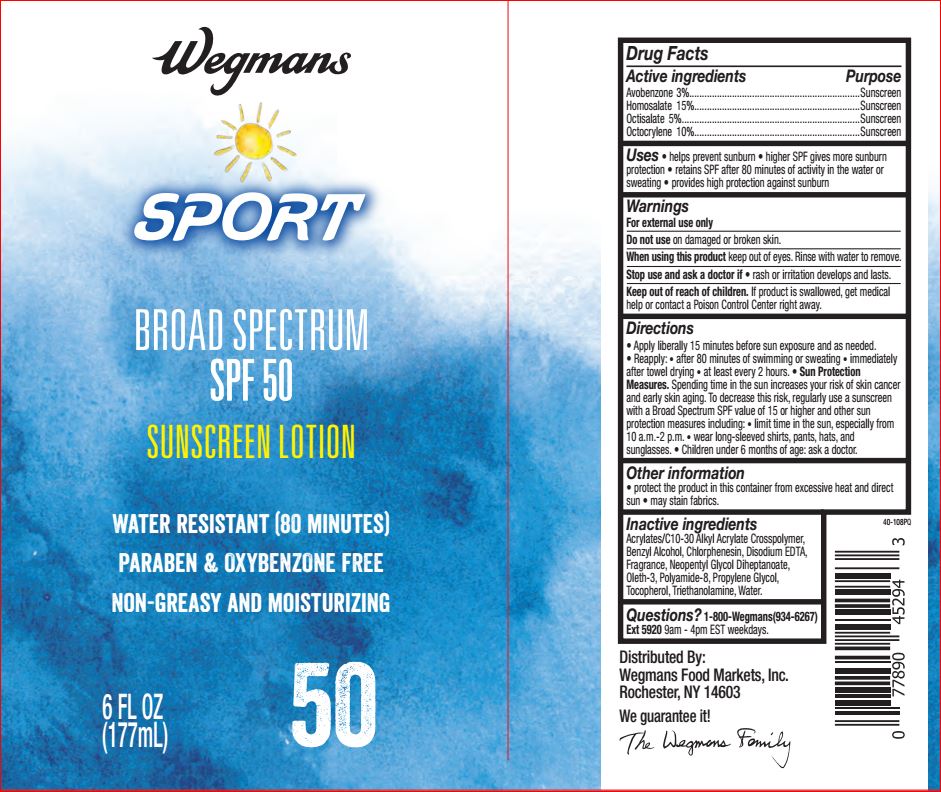 DRUG LABEL: Sport Sunscreen SPF 50
NDC: 47124-114 | Form: LOTION
Manufacturer: Wegman
Category: otc | Type: HUMAN OTC DRUG LABEL
Date: 20180705

ACTIVE INGREDIENTS: Avobenzone 3 g/100 mL; Homosalate 15 g/100 mL; Octisalate 5 g/100 mL; Octocrylene 10 g/100 mL
INACTIVE INGREDIENTS: CARBOMER INTERPOLYMER TYPE A (ALLYL SUCROSE CROSSLINKED); Benzyl Alcohol; Chlorphenesin; EDETATE DISODIUM; Neopentyl Glycol Diheptanoate; Oleth-3; Propylene Glycol; Tocopherol; TROLAMINE; WATER

Drug Facts

WARNINGS AND PRECAUTIONS

Active ingredients Purpose
Avobenzone 3%....................................................................Sunscreen
Homosalate 15%..................................................................Sunscreen
Octisalate 5%.......................................................................Sunscreen
Octocrylene 10%..................................................................Sunscreen

INDICATIONS AND USAGE

Uses • helps prevent sunburn • higher SPF gives more sunburn
protection • retains SPF after 80 minutes of activity in the water or
sweating • provides high protection against sunburn

Warnings
For external use only
Do not use on damaged or broken skin.
When using this product keep out of eyes. Rinse with water to remove.
Stop use and ask a doctor if • rash or irritation develops and lasts.
Keep out of reach of children. If product is swallowed, get medical
help or contact a Poison Control Center right away.

Directions
• Apply liberally 15 minutes before sun exposure and as needed.
• Reapply: • after 80 minutes of swimming or sweating • immediately
after towel drying • at least every 2 hours. • Sun Protection
Measures. Spending time in the sun increases your risk of skin cancer
and early skin aging. To decrease this risk, regularly use a sunscreen
with a Broad Spectrum SPF value of 15 or higher and other sun
protection measures including: • limit time in the sun, especially from
10 a.m.-2 p.m. • wear long-sleeved shirts, pants, hats, and
sunglasses. • Children under 6 months of age: ask a doctor

Other information
• protect the product in this container from excessive heat and direct
sun • may stain fabrics.

Inactive ingredients
Acrylates/C10-30 Alkyl Acrylate Crosspolymer,
Benzyl Alcohol, Chlorphenesin, Disodium EDTA,
Fragrance, Neopentyl Glycol Diheptanoate,
Oleth-3, Polyamide-8, Propylene Glycol,
Tocopherol, Triethanolamine, Water

Questions? 1-800-Wegmans(934-6267)
Ext 5920 9am - 4pm EST weekdays.